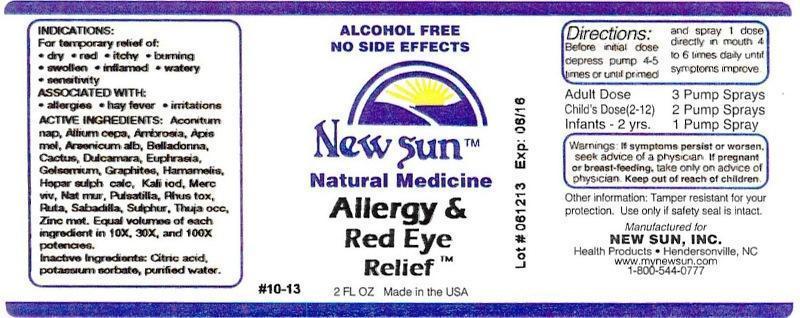 DRUG LABEL: Allergy and Red Eye Relief
NDC: 66579-0079 | Form: LIQUID
Manufacturer: New Sun Inc.
Category: homeopathic | Type: HUMAN OTC DRUG LABEL
Date: 20141020

ACTIVE INGREDIENTS: ACONITUM NAPELLUS 10 [hp_X]/59 mL; ONION 10 [hp_X]/59 mL; AMBROSIA ARTEMISIIFOLIA 10 [hp_X]/59 mL; APIS MELLIFERA 10 [hp_X]/59 mL; ARSENIC TRIOXIDE 10 [hp_X]/59 mL; ATROPA BELLADONNA 10 [hp_X]/59 mL; SELENICEREUS GRANDIFLORUS STEM 10 [hp_X]/59 mL; SOLANUM DULCAMARA TOP 10 [hp_X]/59 mL; EUPHRASIA STRICTA 10 [hp_X]/59 mL; GELSEMIUM SEMPERVIRENS ROOT 10 [hp_X]/59 mL; GRAPHITE 10 [hp_X]/59 mL; HAMAMELIS VIRGINIANA ROOT BARK/STEM BARK 10 [hp_X]/59 mL; CALCIUM SULFIDE 10 [hp_X]/59 mL; POTASSIUM IODIDE 10 [hp_X]/59 mL; MERCURY 10 [hp_X]/59 mL; SODIUM CHLORIDE 10 [hp_X]/59 mL; PULSATILLA VULGARIS 10 [hp_X]/59 mL; TOXICODENDRON PUBESCENS LEAF 10 [hp_X]/59 mL; RUTA GRAVEOLENS FLOWERING TOP 10 [hp_X]/59 mL; SCHOENOCAULON OFFICINALE SEED 10 [hp_X]/59 mL; SULFUR 10 [hp_X]/59 mL; THUJA OCCIDENTALIS LEAFY TWIG 10 [hp_X]/59 mL; ZINC 10 [hp_X]/59 mL
INACTIVE INGREDIENTS: CITRIC ACID MONOHYDRATE; POTASSIUM SORBATE; WATER

Allergy and Red Eye Relief

DOSAGE AND ADMINISTRATION

Directions: Before initial dose depress pump 4-5 times or until primed and spray 1 dose directly in mouth 4 to 6 times daily until symptoms improve.

Adult Dose: 3 Pump Sprays

Child's Dose (2-12): 2 Pump Sprays

Infants - 2 yrs: 1 Pump Spray

WARNINGS

Warnings: If symptoms persist or worsen, seek advice of a physician. If pregnant or breast-feeding, take only on advice of physician.

Keep out of reach of children.

Other information: Tamper resistant for your protection. Use only if safety seal is intact.

PURPOSE

Indications: For temporary relief of: •dry •red •itchy •burning •swollen •inflamed •watery •sensitivity

Associated with: •allergies •hay fever •irritations

ACTIVE INGREDIENT

Active Ingredients: Aconitum napellus, Allium cepa, Ambrosia artemisiaefolia, Apis mellifica, Arsenicum album, Belladonna, Cactus grandiflorus, Dulcamara, Euphrasia officinalis, Gelsemium sempervirens, Graphites, Hamamelis virginiana, Hepar sulphuris calcareum, Kali iodatum, Mercurius vivus, Natrum muriaticum, Pulsatilla, Rhus toxicodendron, Ruta graveolens, Sabadilla, Sulphur, Thuja occidentalis, Zincum metallicum. Equal volumes of each ingredient in 10X, 30X, 100X potencies.

Inactive Ingredient: Citric acid, potassium sorbate, purified water.

Indications: For temporary relief of:

- dry
- red
- itchy
- burning
- swollen
- inflamed
- watery
- sensitivity

Associated with:

- allergies
- hay fever
- irritations